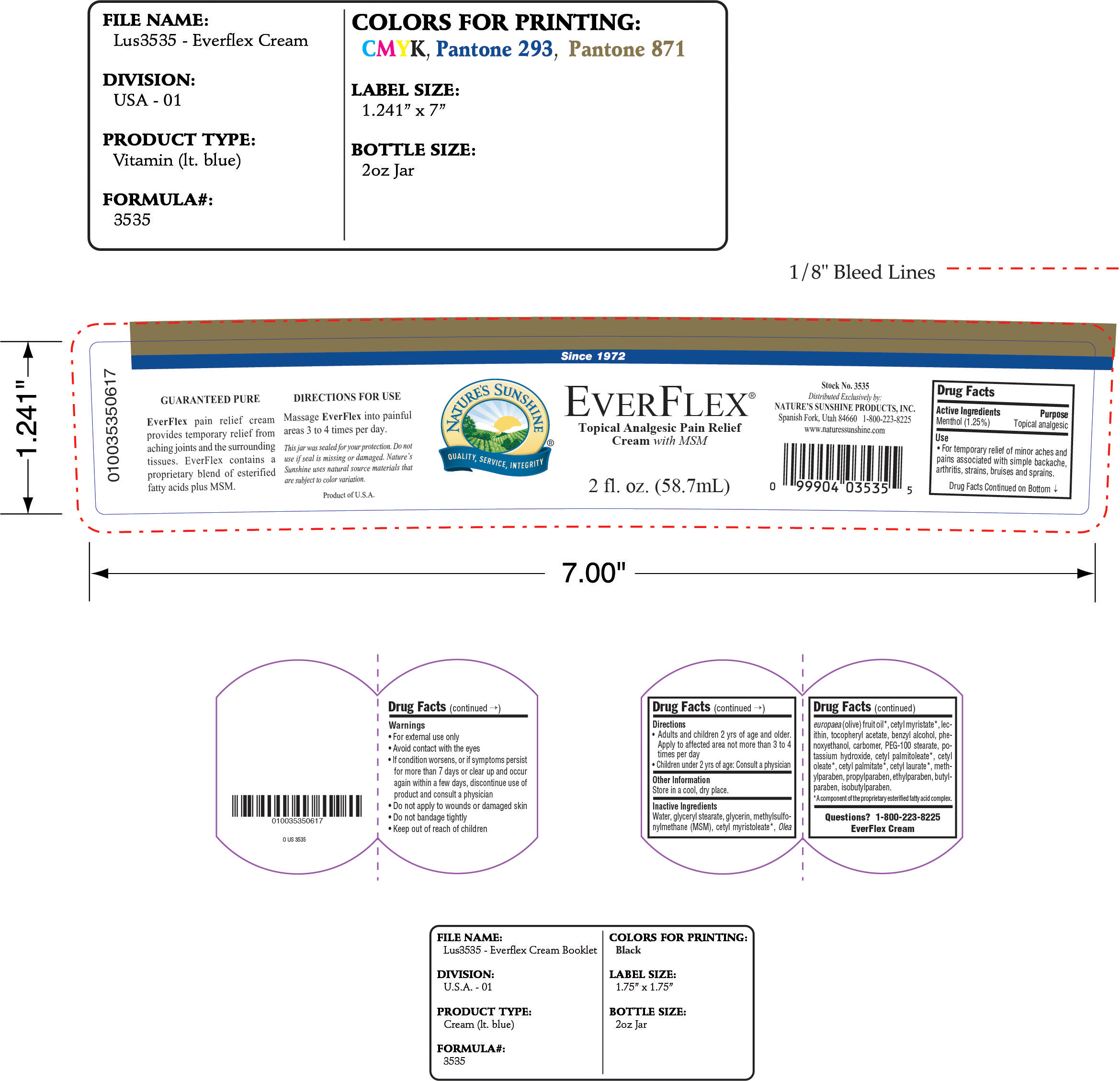 DRUG LABEL: Everflex Topical Analgesic Pain Relief with MSM
NDC: 61582-533 | Form: CREAM
Manufacturer: Natures Sunshine Products, Inc.
Category: otc | Type: HUMAN OTC DRUG LABEL
Date: 20210414

ACTIVE INGREDIENTS: MENTHOL 1.25 g/100 mL
INACTIVE INGREDIENTS: GLYCERYL MONOSTEARATE; GLYCERIN; CETYL MYRISTOLEATE; OLIVE OIL; CETYL MYRISTATE; BENZYL ALCOHOL; PHENOXYETHANOL; PEG-100 STEARATE; POTASSIUM HYDROXIDE; CETYL PALMITOLEATE; CETYL OLEATE; CETYL PALMITATE; METHYLPARABEN; PROPYLPARABEN; ETHYLPARABEN; BUTYLPARABEN; ISOBUTYLPARABEN

Everflex Topical Analgesic Pain Relief with MSM

Active Ingredients Purpose
Menthol 1.25% Topical analgesic

Use

For temporary relief of minor aches and pains associated with with simple backache, arthritis, strains, bruises and sprains.

-Keep out of reach of children

INDICATIONS AND USAGE

-If condition worsens, or if symptoms persist for more than 7 days or clear up and occur again within a few days, discontinue use of product and consult a physician
-Do not apply to wounds or damaged skin
-Do not bandage tightly

Warnings

-For external use only
-Avoid contact with eyes

Directions

- Adults and children 2 yrs of age and and older. Apply to affected area not more than 3 to 4 times per day.
- Children under 2 yrs of age: Consult a physician

INACTIVE INGREDIENT

Inactive Ingredients: Water, Glyceryl Stearate, Glycerin, Methylsulfonylmethane (MSM), Cetyl Myristoleate, Olea Europaea (Olive) Fruit Oil, Cetyl Myristate, Lecithin, Tocopheryl Acetate, Benzyl Alcohol, Phenoxyethanol, Carbomer, PEG-100 Stearate, Potassium Hydroxide, Cetyl Palmitoleate, Cetyl Oleate, Cetyl Palmitate, Cetyl Laurate, Methylparaben, Propylparaben, Ethylparaben, Butylparaben, Isobutylparaben

PACKAGE LABEL

Everflex Topical Analgesic Pain Relief Cream with MSM
2 fl oz. (58.7 mL)